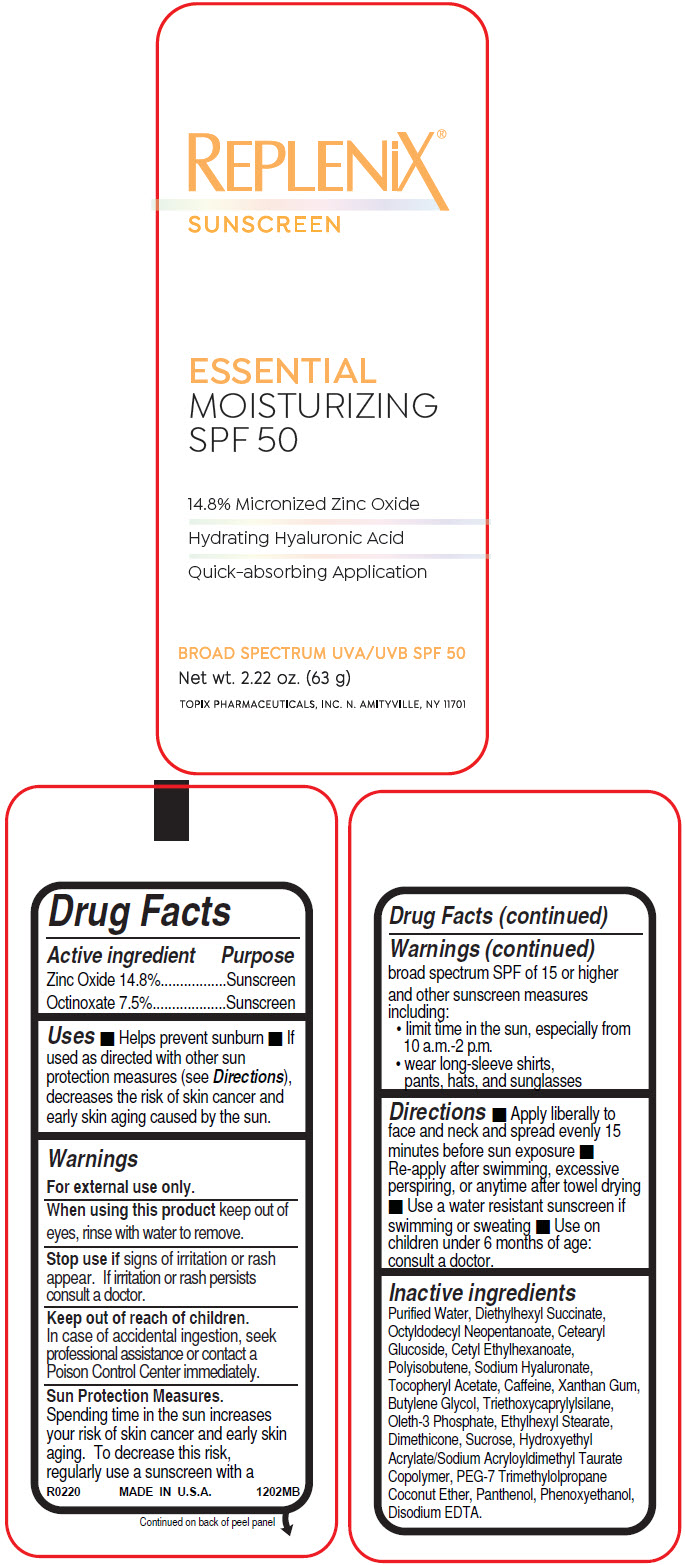 DRUG LABEL: Essential Moisturizing Sunscreen
NDC: 51326-122 | Form: LOTION
Manufacturer: Topiderm, Inc.
Category: otc | Type: HUMAN OTC DRUG LABEL
Date: 20230209

ACTIVE INGREDIENTS: ZINC OXIDE 148 mg/1 g; OCTINOXATE 75 mg/1 g
INACTIVE INGREDIENTS: WATER; DIETHYLHEXYL SUCCINATE; OCTYLDODECYL NEOPENTANOATE; CETEARYL GLUCOSIDE; CETYL ETHYLHEXANOATE; POLYISOBUTYLENE (2300 MW); HYALURONATE SODIUM; .ALPHA.-TOCOPHEROL ACETATE; CAFFEINE; XANTHAN GUM; 1,3-BUTANEDITHIOL; TRIETHOXYCAPRYLYLSILANE; OLETH-3 PHOSPHATE; ETHYLHEXYL STEARATE; DIMETHICONE; SUCROSE; HYDROXYETHYL ACRYLATE/SODIUM ACRYLOYLDIMETHYL TAURATE COPOLYMER (100000 MPA.S AT 1.5%); PEG-7 TRIMETHYLOLPROPANE COCONUT ETHER; PANTHENOL; PHENOXYETHANOL; EDETATE DISODIUM

Essential Moisturizing Sunscreen

Drug Facts

ACTIVE INGREDIENT

Active ingredient | Purpose
Zinc Oxide 14.8% | Sunscreen
Octinoxate 7.5% | Sunscreen

Uses

- Helps prevent sunburn
- If used as directed with other sun protection measures (see Directions), decreases the risk of skin cancer and early skin aging caused by the sun.

Warnings

For external use only.

When using this product keep out of eyes, rinse with water to remove.

Stop use if signs of irritation or rash appear. If irritation or rash persists consult a doctor.

Keep out of reach of children.

In case of accidental ingestion, seek professional assistance or contact a Poison Control Center immediately.

Sun Protection Measures

Spending time in the sun increases your risk of skin cancer and early skin aging. To decrease this risk, regularly use a sunscreen with a broad spectrum SPF of 15 or higher and other sunscreen measures including:

- limit time in the sun, especially from 10 a.m.-2 p.m.
- wear long-sleeve shirts, pants, hats, and sunglasses

Directions

- Apply liberally to face and neck and spread evenly 15 minutes before sun exposure
- Re-apply after swimming, excessive perspiring, or anytime after towel drying
- Use a water resistant sunscreen if swimming or sweating
- Use on children under 6 months of age: consult a doctor.

Inactive ingredients

Purified Water, Diethylhexyl Succinate, Octyldodecyl Neopentanoate, Cetearyl Glucoside, Cetyl Ethylhexanoate, Polyisobutene, Sodium Hyaluronate, Tocopheryl Acetate, Caffeine, Xanthan Gum, Butylene Glycol, Triethoxycaprylylsilane, Oleth-3 Phosphate, Ethylhexyl Stearate, Dimethicone, Sucrose, Hydroxyethyl Acrylate/Sodium Acryloyldimethyl Taurate Copolymer, PEG-7 Trimethylolpropane Coconut Ether, Panthenol, Phenoxyethanol, Disodium EDTA.

PRINCIPAL DISPLAY PANEL - 63 g Bottle Label

REPLENiX®
SUNSCREEN

ESSENTIAL
MOISTURIZING
SPF 50

14.8% Micronized Zinc Oxide
Hydrating Hyaluronic Acid
Quick-absorbing Application

BROAD SPECTRUM UVA/UVB SPF 50

Net wt. 2.22 oz. (63 g)

TOPIX PHARMACEUTICALS, INC. N. AMITYVILLE, NY 11701